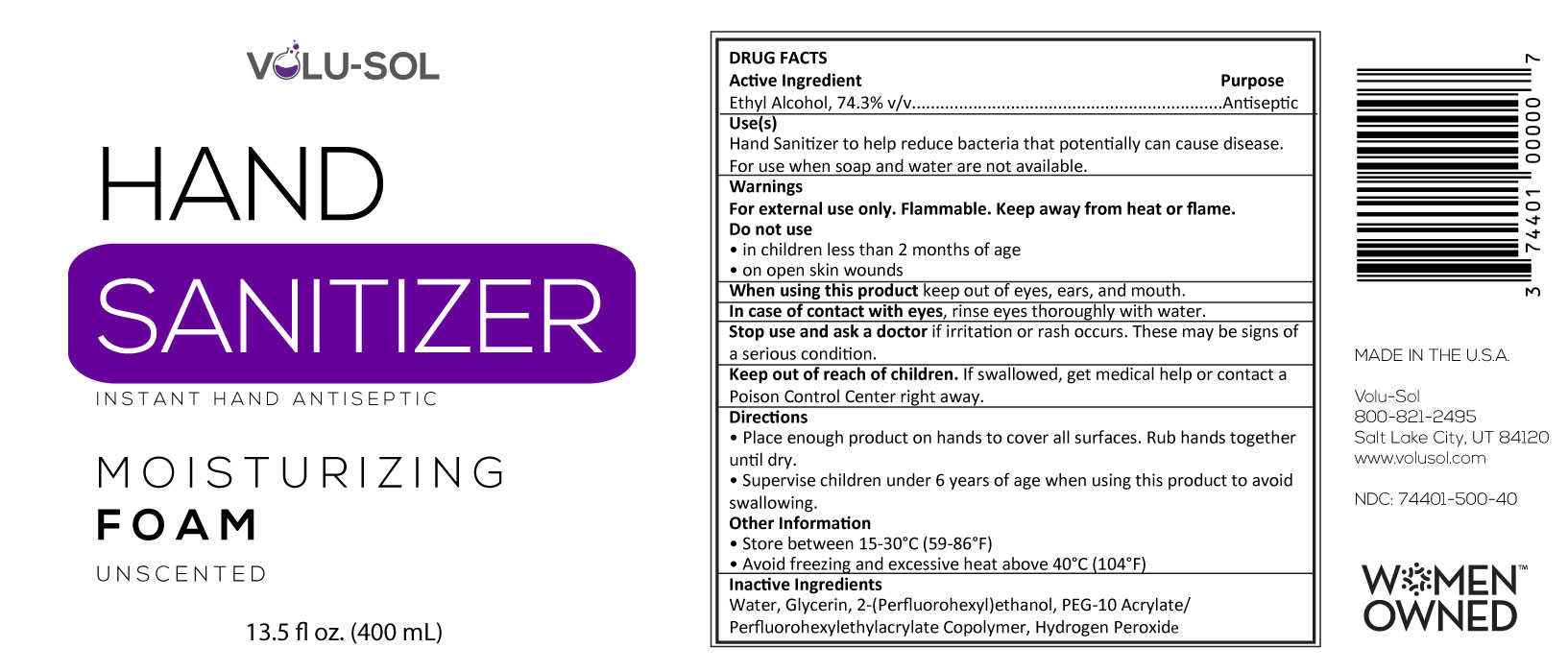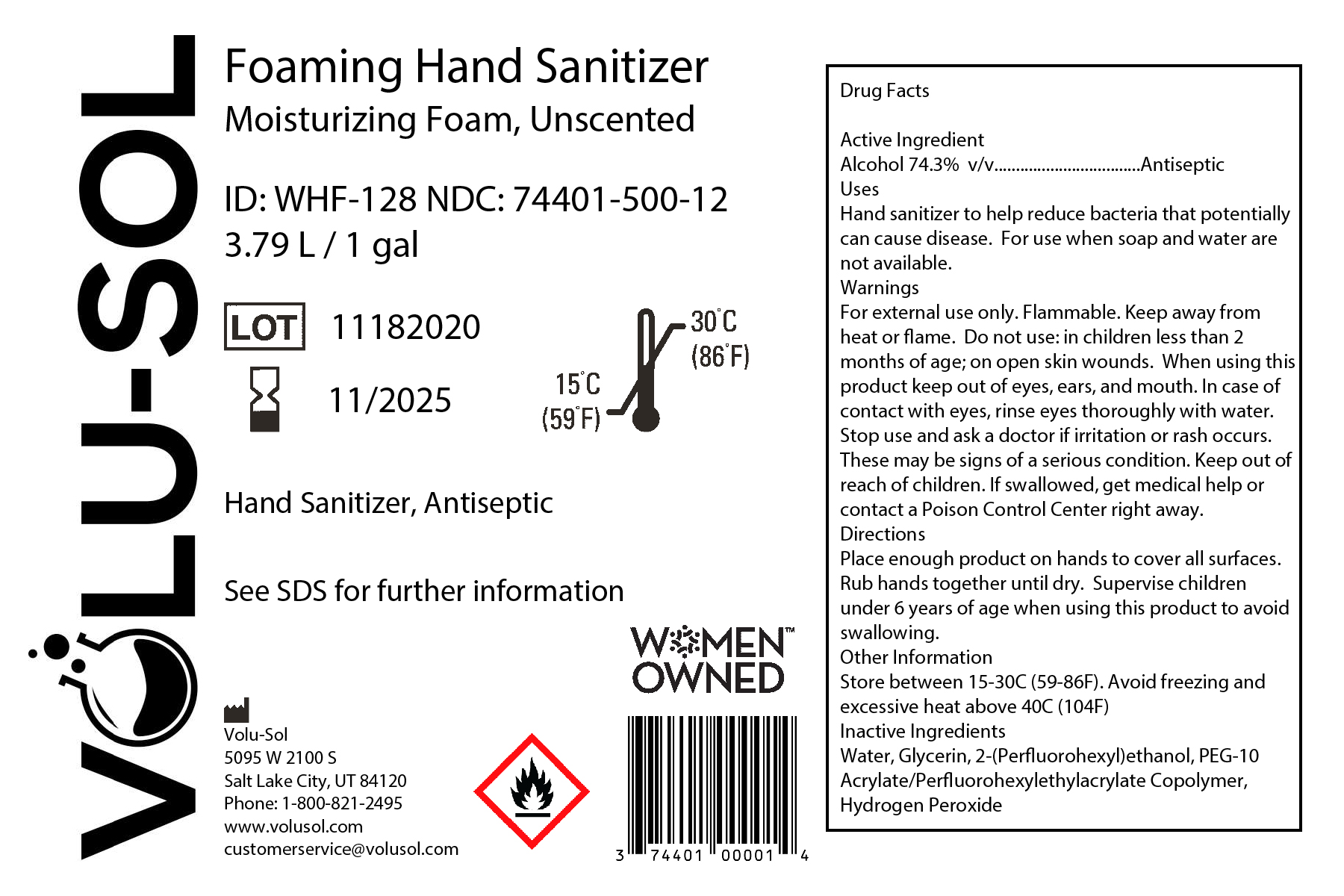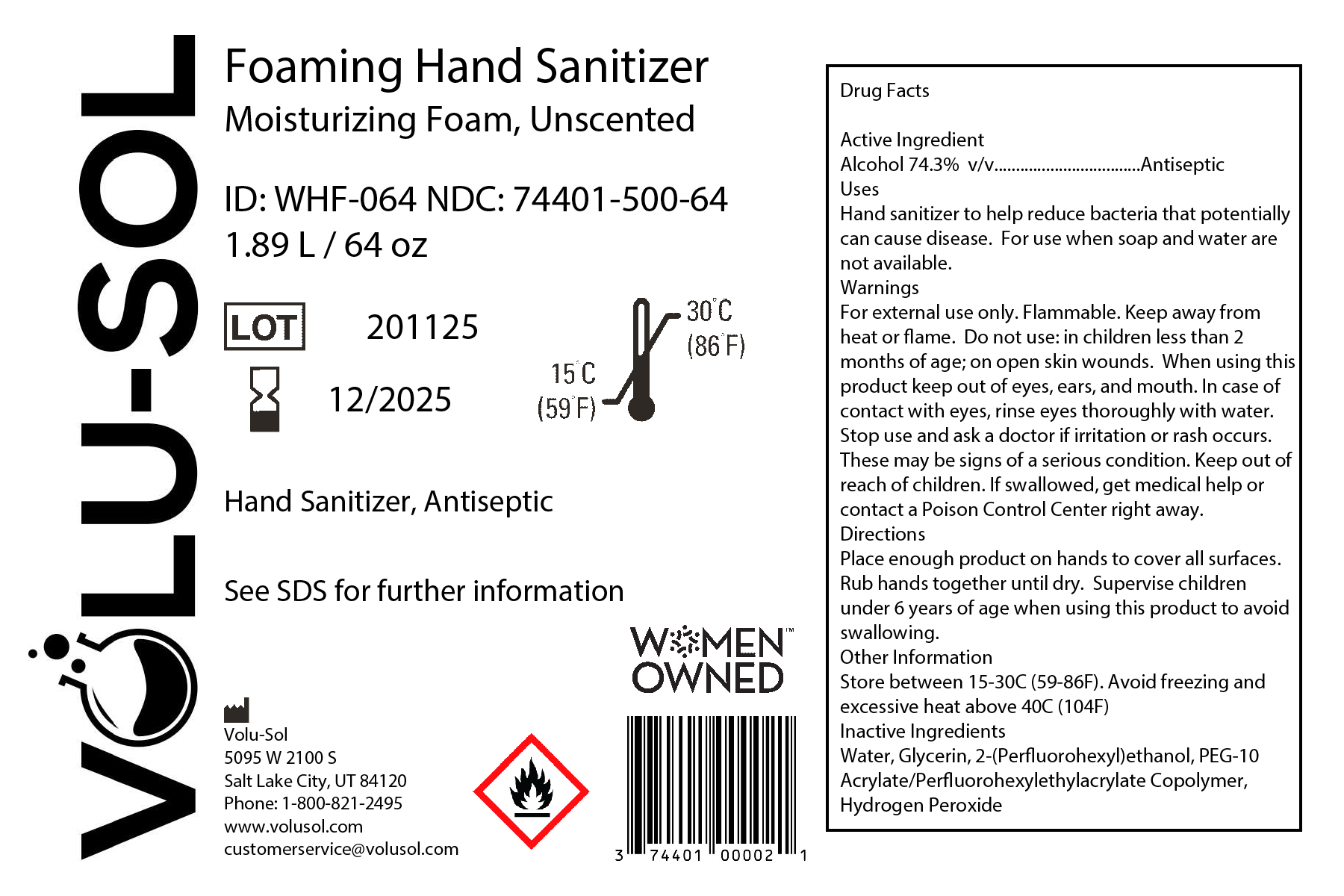 DRUG LABEL: Moisturizing Foam Hand Sanitizer
NDC: 74401-500 | Form: LIQUID
Manufacturer: Volu-Sol
Category: otc | Type: HUMAN OTC DRUG LABEL
Date: 20250113

ACTIVE INGREDIENTS: ALCOHOL 74.3 mL/100 mL
INACTIVE INGREDIENTS: PEG-10 ACRYLATE/PERFLUOROHEXYLETHYL ACRYLATE COPOLYMER 0.165 mL/100 mL; GLYCERIN 1.35 mL/100 mL; HYDROGEN PEROXIDE 0.125 mL/100 mL; WATER; 2-(PERFLUOROHEXYL)ETHANOL 0.165 mL/100 mL

Active Ingredient(s)

Alcohol 74.3% v/v. Purpose: Antiseptic

Purpose

Antiseptic, Hand Sanitizer

Use

Hand Sanitizer to help reduce bacteria that potentially can cause disease. For use when soap and water are not available.

Warnings

For external use only. Flammable. Keep away from heat or flame

Do not use

- in children less than 2 months of age
- on open skin wounds

When using this product keep out of eyes, ears, and mouth. In case of contact with eyes, rinse eyes thoroughly with water.
Stop use and ask a doctor if irritation or rash occurs. These may be signs of a serious condition.
Keep out of reach of children. If swallowed, get medical help or contact a Poison Control Center right away.

Stop use and ask a doctor if irritation or rash occurs. These may be signs of a serious condition.

Keep out of reach of children. If swallowed, get medical help or contact a Poison Control Center right away.

Directions

- Place enough product on hands to cover all surfaces. Rub hands together until dry.
- Supervise children under 6 years of age when using this product to avoid swallowing.

Other information

- Store between 15-30C (59-86F)
- Avoid freezing and excessive heat above 40C (104F)

Inactive ingredients

Water, Glycerin, 2-(Perfluorohexyl)ethanol, PEG-10 Acrylate/Perfluorohexylethylacrylate Copolymer, Hydrogen Peroxide

Package Label - Principal Display Panel

1893 mL NDC: 74401-500-64

400 mL NDC: 74401-500-40

3785 mL NDC: 74401-500-12